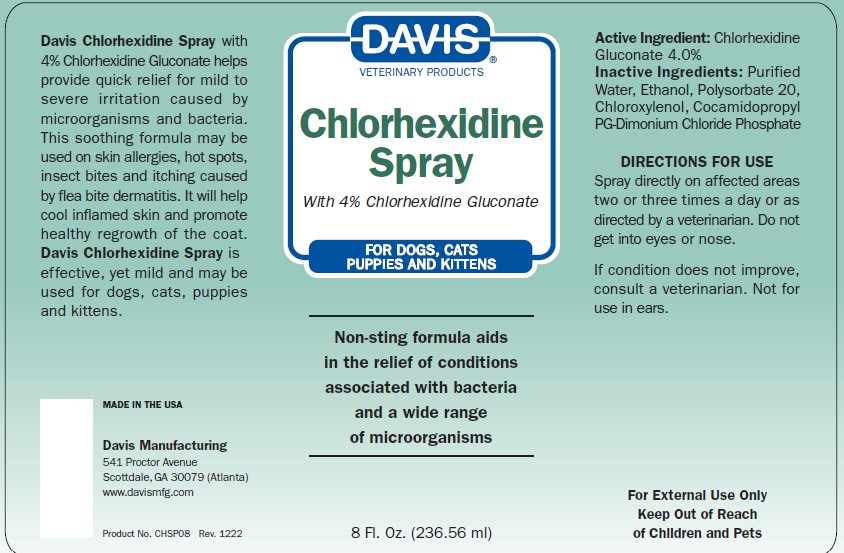 DRUG LABEL: Davis Chlorhexidine
NDC: 62570-030 | Form: SPRAY
Manufacturer: Davis Manufacturing and Packaging Inc
Category: animal | Type: OTC ANIMAL DRUG LABEL
Date: 20230504

ACTIVE INGREDIENTS: CHLORHEXIDINE GLUCONATE 4 g/100 g
INACTIVE INGREDIENTS: ALCOHOL; TERT-BUTYL ALCOHOL; POLYSORBATE 20; WATER; COCAMIDOPROPYL PROPYLENE GLYCOL-DIMONIUM CHLORIDE PHOSPHATE

Davis Chlorhexidine Spray

Chlorhexidine Spray

Davis Chlorhexidine Spray with 4% Chlorhexidine Gluconate helps provide quick relief for mild to severe irritation caused by microorganisms and bacteria. This soothing formula may be used on skin allergies, hot spots, insect bites and itching caused by fleabite dermatitis. It will cool inflamed skin and promote healthy regrowth of the coat. Davis Chlorhexidine Spray is effective, yet mild and may be used for dogs, cats, puppies, kittens, horses and foals.

Environmentally Friendly

MADE INTHE USA

Davis Manufacturing

541 Proctor Avenue

Atlanta/Scottdale, GA 30079

www.davismfg.com

Product No. CHSP08 Rev. 0209

Directions for Use

Spray directly on affected areas two to three times a day or as directed by a veterinarian. Not for use in ears.

ACTIVE INGREDIENT

Chlorhexidine Gluconate 4%

INACTIVE INGREDIENT

Ingredients: Phospholipid Complex, PCMX, SDA 40, Polyoxyethylene sorbatan Monolaurate, Purified Water

KEEP OUT OF REACH OF CHILDREN

For External Use Only

Keep Out Of Reach Of Children

Principal Display Panel

Davis Veterinary Products

Chlorhexidine Spray

With 4% Chlorhexidine Gluconate

FOR DOGS, CATS, PUPPIES AND KITTENS

Non-sting formula aids in the relief of conditions associated with bacteria and a wide range of microorganisms

8 Fl. Oz. (236.56 ml)